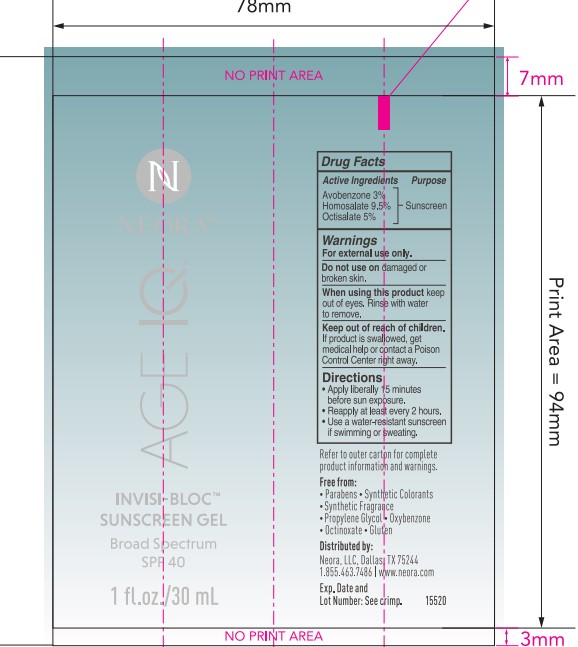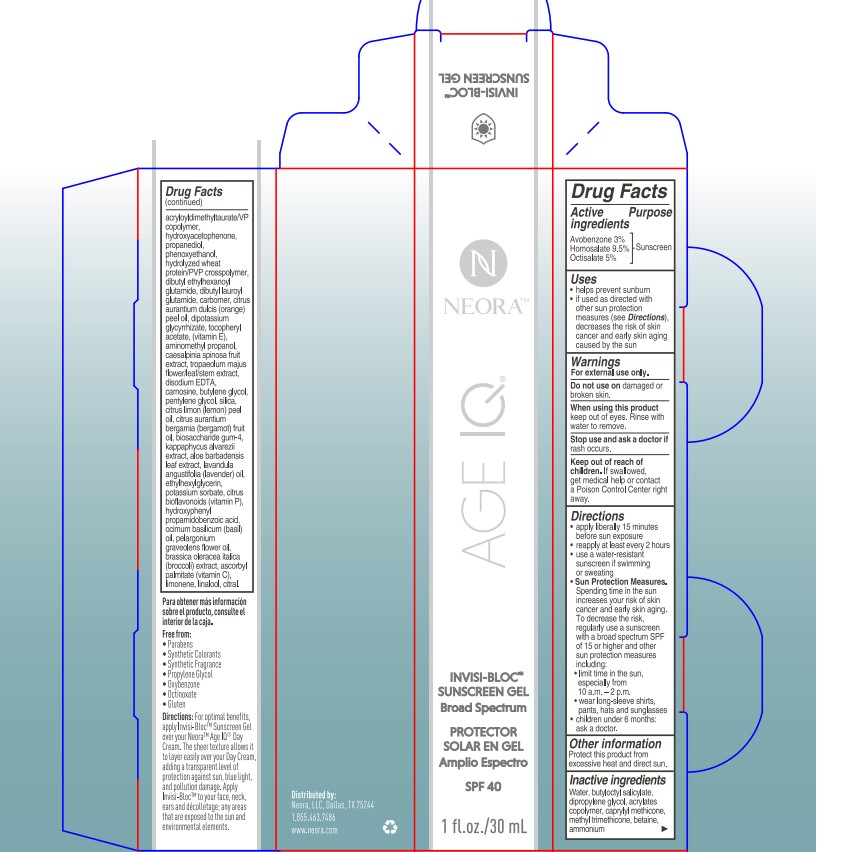 DRUG LABEL: NEORA Invisibloc Sunscreen Gel Broad Spectrum SPF40
NDC: 68577-157 | Form: LOTION
Manufacturer: COSMAX USA, CORPORATION
Category: otc | Type: HUMAN OTC DRUG LABEL
Date: 20241226

ACTIVE INGREDIENTS: AVOBENZONE 3 mg/100 mg; HOMOSALATE 9.5 mg/100 mg; OCTISALATE 5 mg/100 mg
INACTIVE INGREDIENTS: CITRUS LIMON FLOWERING TOP OIL; KAPPAPHYCUS ALVAREZII; CITRAL; EDETATE DISODIUM ANHYDROUS; ASCORBYL PALMITATE; HYDROXYPHENYL PROPAMIDOBENZOIC ACID; ETHYLHEXYLGLYCERIN; LIMONENE, (+/-)-; CARNOSINE; SILICON DIOXIDE; TROPAEOLUM MAJUS FLOWER; BIOSACCHARIDE GUM-4; ALOE VERA LEAF; BUTYLENE GLYCOL; PENTYLENE GLYCOL; PELARGONIUM GRAVEOLENS FLOWER OIL; BROCCOLI SPROUT; LINALOOL, (+/-)-; LAVENDER OIL; CITRUS BIOFLAVONOIDS; WATER; BUTYLOCTYL SALICYLATE; DIPROPYLENE GLYCOL; BUTYL ACRYLATE/METHYL METHACRYLATE/METHACRYLIC ACID COPOLYMER (18000 MW); CAPRYLYL TRISILOXANE; METHYL TRIMETHICONE; BASIL OIL; BETAINE; AMMONIUM ACRYLOYLDIMETHYLTAURATE/VP COPOLYMER; PHENOXYETHANOL; HYDROLYZED WHEAT PROTEIN (ENZYMATIC, 3000 MW); DIBUTYL LAUROYL GLUTAMIDE; CITRUS AURANTIUM FRUIT OIL; HYDROXYACETOPHENONE; PROPANEDIOL; DIBUTYL ETHYLHEXANOYL GLUTAMIDE; CARBOMER HOMOPOLYMER, UNSPECIFIED TYPE; ORANGE OIL; .ALPHA.-TOCOPHEROL ACETATE; GLYCYRRHIZINATE DIPOTASSIUM; POTASSIUM SORBATE; BRASSICA OLERACEA VAR. BOTRYTIS WHOLE; AMINOMETHYLPROPANOL; CAESALPINIA SPINOSA FRUIT POD

NEORA Invisi-bloc Sunscreen Gel Broad Spectrum SPF40

Active Ingredients

Avobenzone 3%

Homosalate 9.5%

Octisalate 5%

Purpose

Sunscreen

USES

- helps prevent sunburn
- if used as directed with other sun protection measures (see Directions), decreases the risk of skin cancer and early skin aging cause by the sun

Warnings

For extenal use only

Do not useon damaged or broken skin

WHEN USING

When using this productkeep out of eyes. Rinse with water to remove.

Stop use and ask a doctor ifrash occurs

Keep out of reach of children.If swallowed, get medical help or contact a Poison Control Center right away.

DIRECTIONS

- apply liberrally 15 minutes before sun exposure
- reapply at least every 2 hours
- use a water-resistant sunscreen if swimming or sweating
- Sun Protection Measures.Spending time in the sun

increases your risk of skin cancer and early skin aging. To decrease

this risk, regularly use a sunscreen with a Broad Spectrum SPF

value of 15 or higher and other sun protection measures including:

- limit time in the sun, especially from 10 a.m. - 2 p.m.
- wear long-sleeved shirts, pants, hats, and sunglasses
- children under 6 months of age:ask a doctor

OTHER INFORMATION

- Protect the product in this container from excessive heat and direct sun

Inactive ingredients:

Water, butyloctyl salicylate, dipropylene glycol, acrylates copolymer, caprylyl methicone, methyl trimethicone, betaine, ammonium acryloyldimethyltaurate/VP copolymer, hydroxyacetophenone, propanediol, phenoxyethanol, hydrolyzed wheat protein/PVP crosspolymer, dibutyl ethylhexanoyl glutamide, dibutyl lauroyl glutamide, carbomer, citrus aurantium dulcis (orange) peel oil, dipotassium glycyrrhizate, tocopheryl acetate, (vitamin E), aminomethyl propanol, caesalpinia spinosa fruit extract, tropaeolum majus flower/leaf/stem extract, disodium EDTA, carnosine, butylene glycol, pentylene glycol, silica, citrus limon (lemon) peel oil, citrus aurantium bergamia (bergamot) fruit oil, biosaccharide gum-4, kappaphycus alvarezii extract, aloe barbadensis leaf extract, lavandula angustifolia (lavender) oil, ethylhexylglycerin, potassium sorbate, citrus bioflavonoids (vitamin P), hydroxyphenyl propamidobenzoic acid, ocimum basilicum (basil) oil, pelargonium graveolens flower oil, brassica oleracea italica (broccoli) extract, ascorbyl palmitate (vitamin C), limonene, linalool, citral.

PACKAGE LABEL

Primary Packaging

Secondary Package